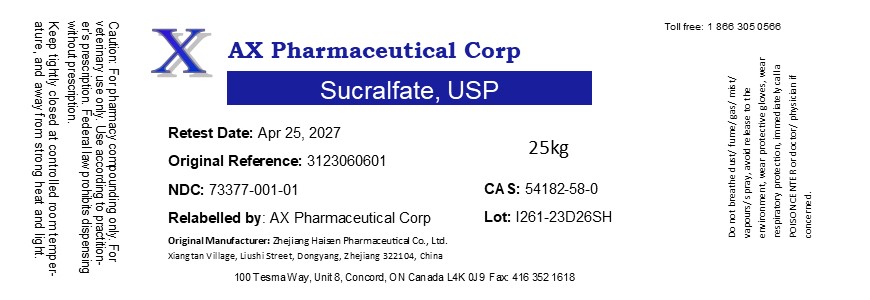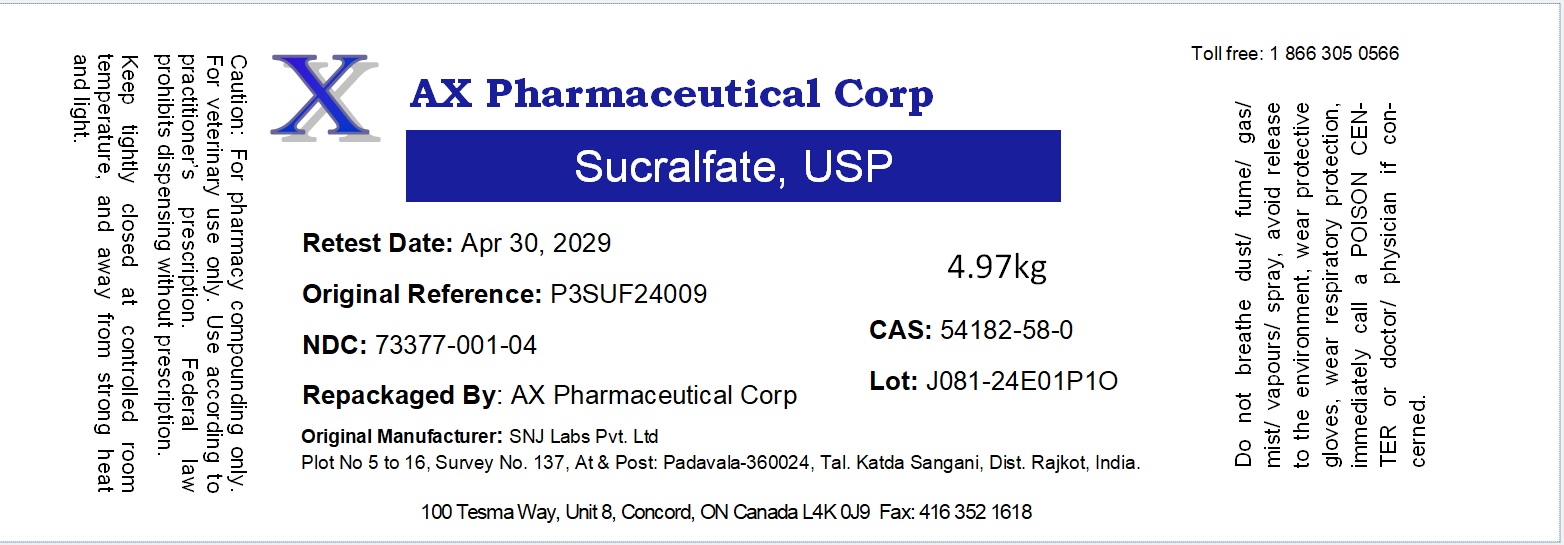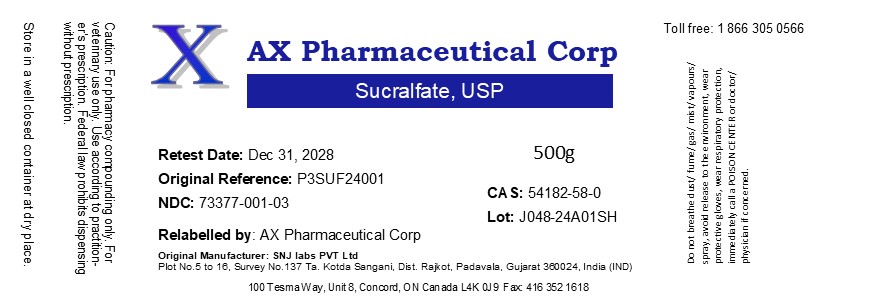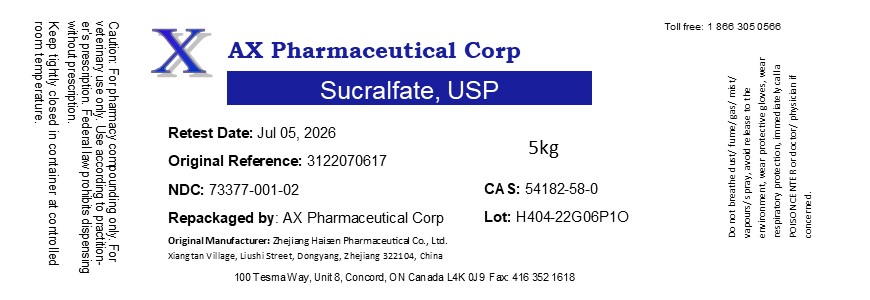 DRUG LABEL: Sucralfate
NDC: 73377-001 | Form: POWDER
Manufacturer: AX Pharmaceutical Corp
Category: other | Type: BULK INGREDIENT - ANIMAL DRUG
Date: 20241015

ACTIVE INGREDIENTS: SUCRALFATE 1 kg/1 kg

Sucralfate